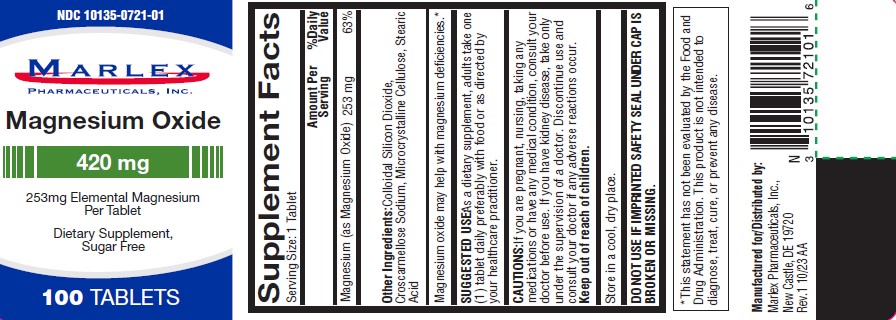 DRUG LABEL: magnesium oxide
NDC: 10135-721 | Form: TABLET
Manufacturer: Marlex Pharmaceuticals Inc.
Category: otc | Type: HUMAN OTC DRUG LABEL
Date: 20251114

ACTIVE INGREDIENTS: MAGNESIUM OXIDE 420 mg/1 1
INACTIVE INGREDIENTS: MICROCRYSTALLINE CELLULOSE; STEARIC ACID; SILICON DIOXIDE; CROSCARMELLOSE SODIUM

MAGNESIUM OXIDE- magnesium oxide tablet

ACTIVE INGREDIENT (In each tablet)

Magnesium Oxide 420 mg

Purpose

Dietary Supplement

Supplement Facts

Serving Size | 1 Tablet
Magnesium (as Magnesium Oxide)
Amount per Serving | 253mg
% Daily value | 63%

Other Ingredients

Colloidal silicon dioxide, Croscarmellose sodium, microcrystalline cellulose, stearic acid

Magnesium oxide may help with magnesium deficiencies.*

SUGGESTED USE

As a dietary supplements, adult take one (1) tablet daily preferably with food or as directed by your healthcare practitioner.

CAUTIONS

If you are pregnant, nursing, taking any medications or have any medical condition, consult your doctor before use. If you have any kidney disease, take only under the supervision of a doctor. Discontinue use and consult your doctor if any adverse reactions occur.

Keep out of reach of children.

Store in a cool, dry place.

DO NOT USE IF IMPRINTED SAFETY SEAL UNDER CAP IS BROKEN OR MISSING.

* These statement has not been evaluated by the Food and Drug Administration. This product is not intended to diagnose, treat, cure, or prevent any disease.

Manufactured for/ Distributed by:

Marlex Pharmaceuticals, Inc.,

New Castle, DE 19720

Rev.1 10/23 AA

PRINCIPAL DISPLAY PANEL

NDC 10135-0721-01

Magnesium Oxide 420 mg

100 TABLETS